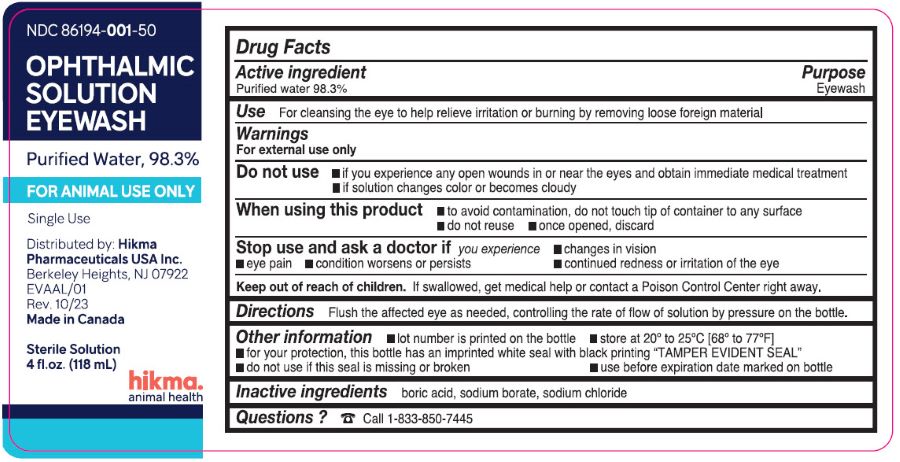 DRUG LABEL: Opthalmic Solution Eyewash
NDC: 86194-001 | Form: SOLUTION
Manufacturer: Hikma Pharmaceuticals USA Inc.
Category: animal | Type: OTC ANIMAL DRUG LABEL
Date: 20250120

ACTIVE INGREDIENTS: WATER 929 g/946 mL
INACTIVE INGREDIENTS: BORIC ACID; SODIUM CHLORIDE; SODIUM BORATE

Hikma Opthalmic Solution Eyewash
Purified Water, 98.3%
Ophthalmic Solution
Eyewash

Drug Facts

Active ingredient

Purified water 98.3%

Purpose

Eyewash

Use

For cleansing the eye to help relieve irritation or burning by removing loose foreign material

Warnings

For external use only

Do not use

- if you experience any open wounds in or near the eyes and obtain immediate medical treatment
- if solution changes color or becomes cloudy

When using this product

- to avoid contamination, do not touch tip of container to any surface
- do not reuse
- once opened, discard

Stop use and ask a doctor if you experience

- changes in vision
- eye pain
- condition worsens or persists
- continued redness or irritation of the eye

Keep out of reach of children. If swallowed, get medical help or contact a Poison Control Center right away.

Directions

Flush the affected eye as needed, controlling the rate of flow of solution by pressure on the bottle.

Other information

- lot number is printed on the bottle
- store at 20° to 25° C [68° to 77° F]
- for your protection, this bottle has an imprinted white seal with black printing "TAMPER EVIDENT SEAL"
- do not use if this seal is missing or broken
- use before expiration date marked on bottle

Inactive ingredients

boric acid, sodium borate, sodium chloride

Questions ?

☎ Call 833-850-7445

Distributed by:
Hikma Pharmaceuticals USA Inc.
Berkeley Heights, NJ 07922

PRINCIPAL DISPLAY PANEL - 118 mL Bottle Label

NDC 86194-001-50

OPHTHALMIC
SOLUTION
EYEWASH

Purified Water, 98.3%

FOR ANIMAL USE ONLY

Single Use

Distributed by: Hikma

Pharmaceuticals USA Inc.

Berkeley Heights, NJ 07922

EVAAL/01

Rev. 10/23

Made in Canada

Sterile Solution

4 fl.oz. (118 mL)

hikma.

animal health